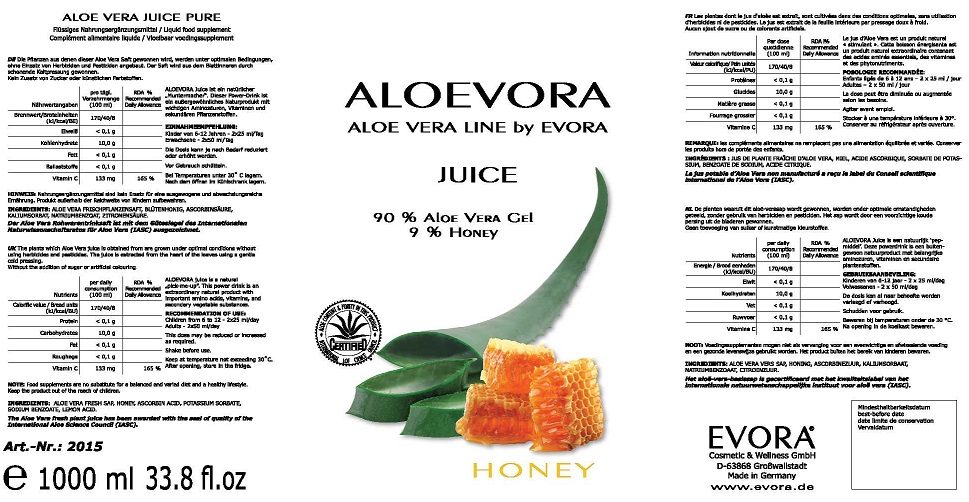 DRUG LABEL: ALOEVORA JUICE
NDC: 70822-101 | Form: SOLUTION
Manufacturer: EVORA Cosmetic and Wellness GmbH
Category: other | Type: Dietary Supplement
Date: 20190628

ACTIVE INGREDIENTS: ALOE VERA LEAF 90 g/100 mL; HONEY 9 g/100 mL
INACTIVE INGREDIENTS: ASCORBIC ACID; POTASSIUM SORBATE; SODIUM BENZOATE; LEMON

STATEMENT OF IDENTITY

ALOEVORA

ALOE VERA LINE BY EVORA

JUICE

90% ALOE VERA GEL

9% HONEY